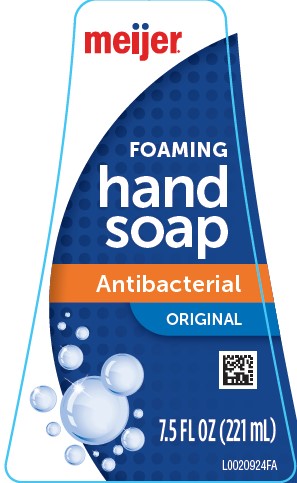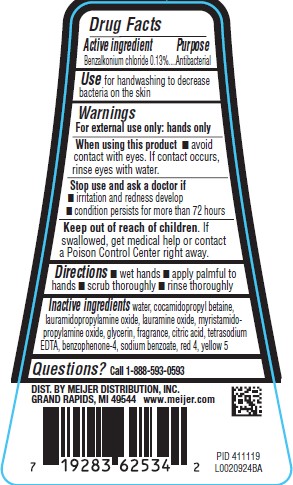 DRUG LABEL: Hand Wash
NDC: 41250-661 | Form: LIQUID
Manufacturer: Meijer, Inc.
Category: otc | Type: HUMAN OTC DRUG LABEL
Date: 20260219

ACTIVE INGREDIENTS: BENZALKONIUM CHLORIDE 1.3 mg/1 mL
INACTIVE INGREDIENTS: COCAMIDOPROPYL BETAINE; LAURAMIDOPROPYLAMINE OXIDE; LAURAMINE OXIDE; MYRISTAMIDOPROPYLAMINE OXIDE; GLYCERIN; CITRIC ACID MONOHYDRATE; EDETATE SODIUM; SULISOBENZONE; WATER; SODIUM BENZOATE; FD&C RED NO. 4; FD&C YELLOW NO. 5

Meijer 466.001/466AB
Antibacterial Foaming Hand Wash

Active ingredient

Benzalkonium chloride 0.13%

purpose

Antibacterial

Use

for handwashing to decrease bacteria on the skin

Warnings

For external use only: hands only

When using this product

- avoid contact with eyes. If contact occurs, rinse eyes thoroughly with water.

Stop use and ask a doctor if

- irritation and redness develop
- condition persists for more than 72 hours

Keep out of reach of children

if swallowed, get medical help or contact a Poison Control Center right away.

Directions

- wet hands
- apply palmful to hands
- scrub thoroughly
- rinse thoroughly

Inactive ingredients

water, cocamidopropyl betaine, lauramidopropylamine oxide, lauramine oxide, myristamidopropylamine oxide, glycerin, fragrance, citric acid, tetrasodium EDTA, benzophenone-4, sodium benzoate, red 4, yellow 5

Questions?

Call 1-888-593-0593

Adverse reactions

DIST. BY MEIJER DISTRIBUTION, INC

GRAND RAPIDS, MI 49544

www.meijer.com

principal display panel

meijer®

FOAMING

hand

soap

Antibacterial

ORIGINAL

7.5 FL OZ (221 mL)